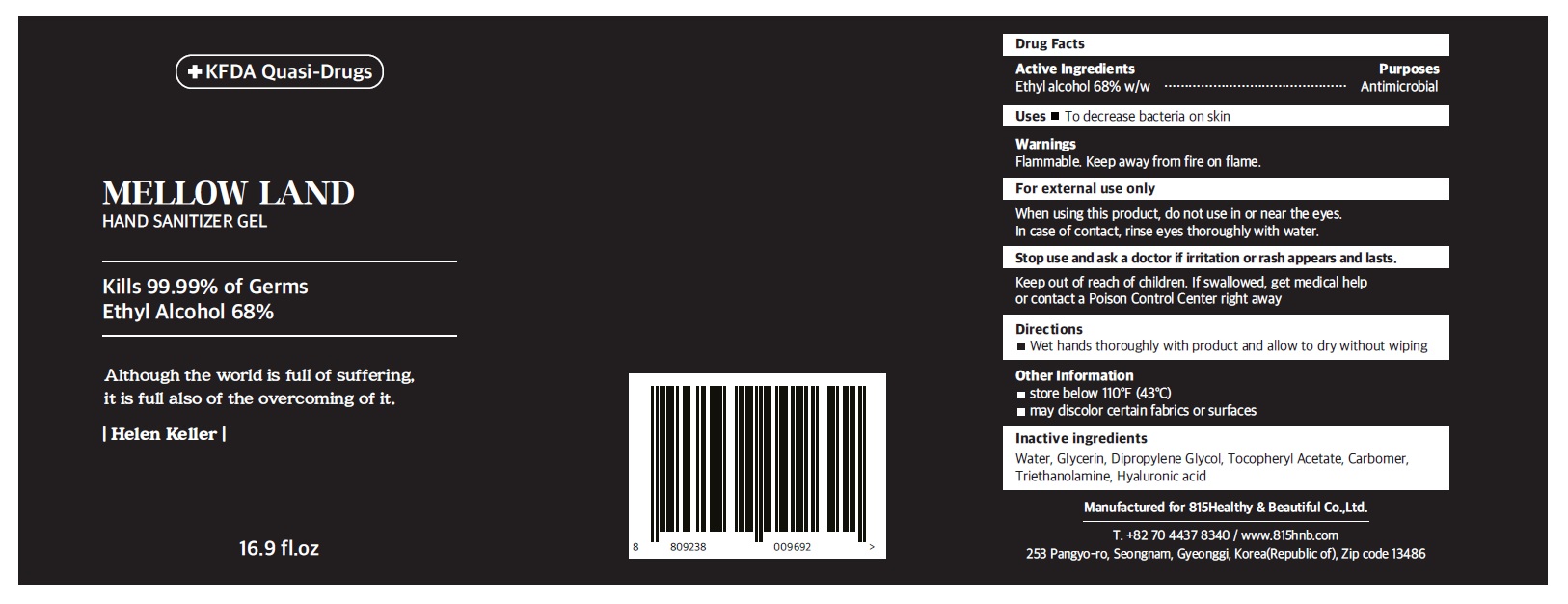 DRUG LABEL: Mellow Land Hand Sanitizer gel
NDC: 79210-002 | Form: GEL
Manufacturer: 815Healthy & Beautiful Co.,Ltd.
Category: otc | Type: HUMAN OTC DRUG LABEL
Date: 20200623

ACTIVE INGREDIENTS: ALCOHOL 0.68 mL/1 mL
INACTIVE INGREDIENTS: WATER; GLYCERIN; DIPROPYLENE GLYCOL; .ALPHA.-TOCOPHEROL ACETATE; CARBOMER INTERPOLYMER TYPE A (ALLYL SUCROSE CROSSLINKED); TROLAMINE; HYALURONIC ACID

79210-002_Mellow Land Hand Sanitizer Gel

Active ingredient

Ethyl alcohol 68% w/w

Purpose

Antimicrobial

Use

- To decrease bacteria on the skin

Warnings

Flammable. Keep away from fire or flame.

For external use only

When using this product do not use in or near the eyes. In case of contact, rinse eyes thoroughly with water.

Stop use and ask a doctor if irritation or rash appears and lasts

Keep out of reach of children. If swallowed, get medical help or contact a Poison Control Center right away.

Directions

Wet hands thoroughly with product and allow to dry without wiping

Other information

- Store below 110°F (43°C)
- May discolor certain fabrics or surfaces

Inactive ingredients

Water, Glycerin, Dipropylene Glycol, Tocopheryl Acetate, Carbomer, Triethanolamine, Hyaluronic acid